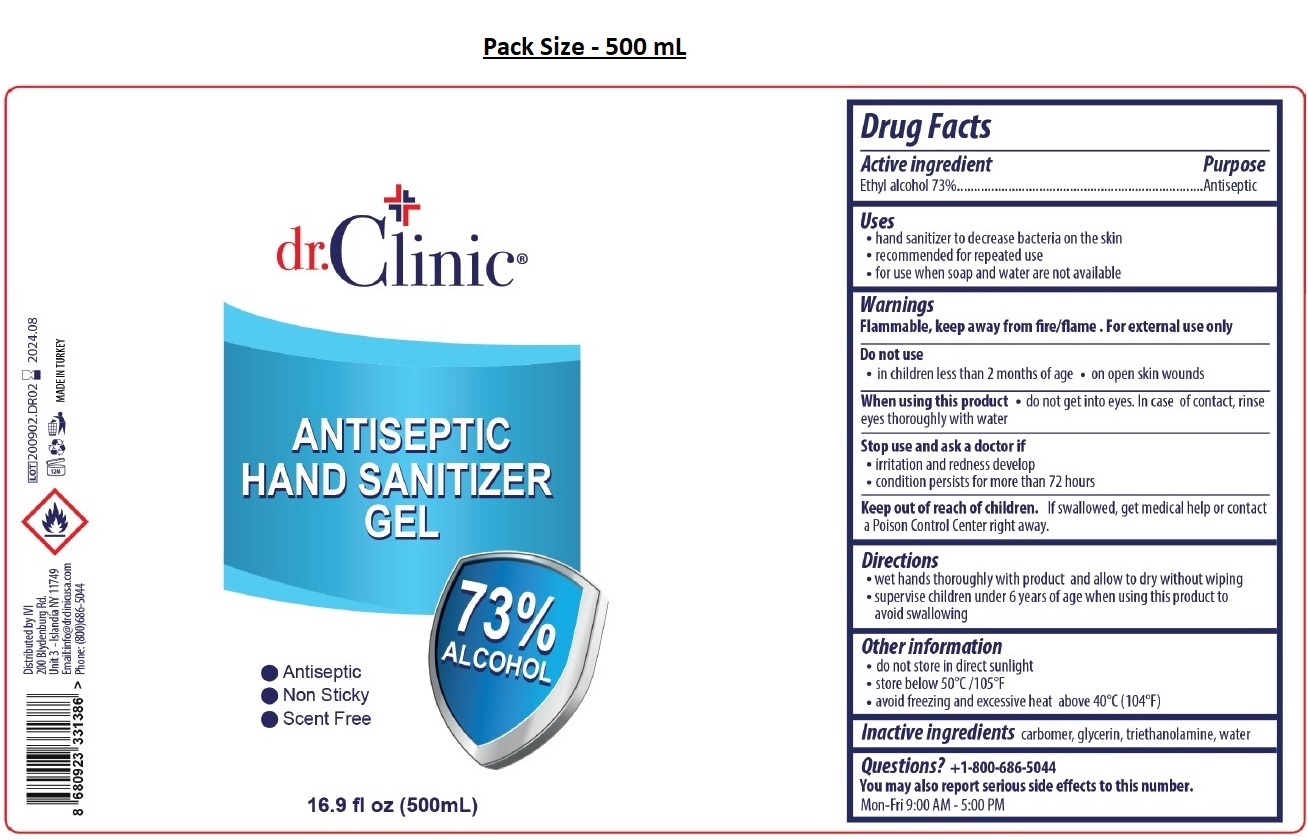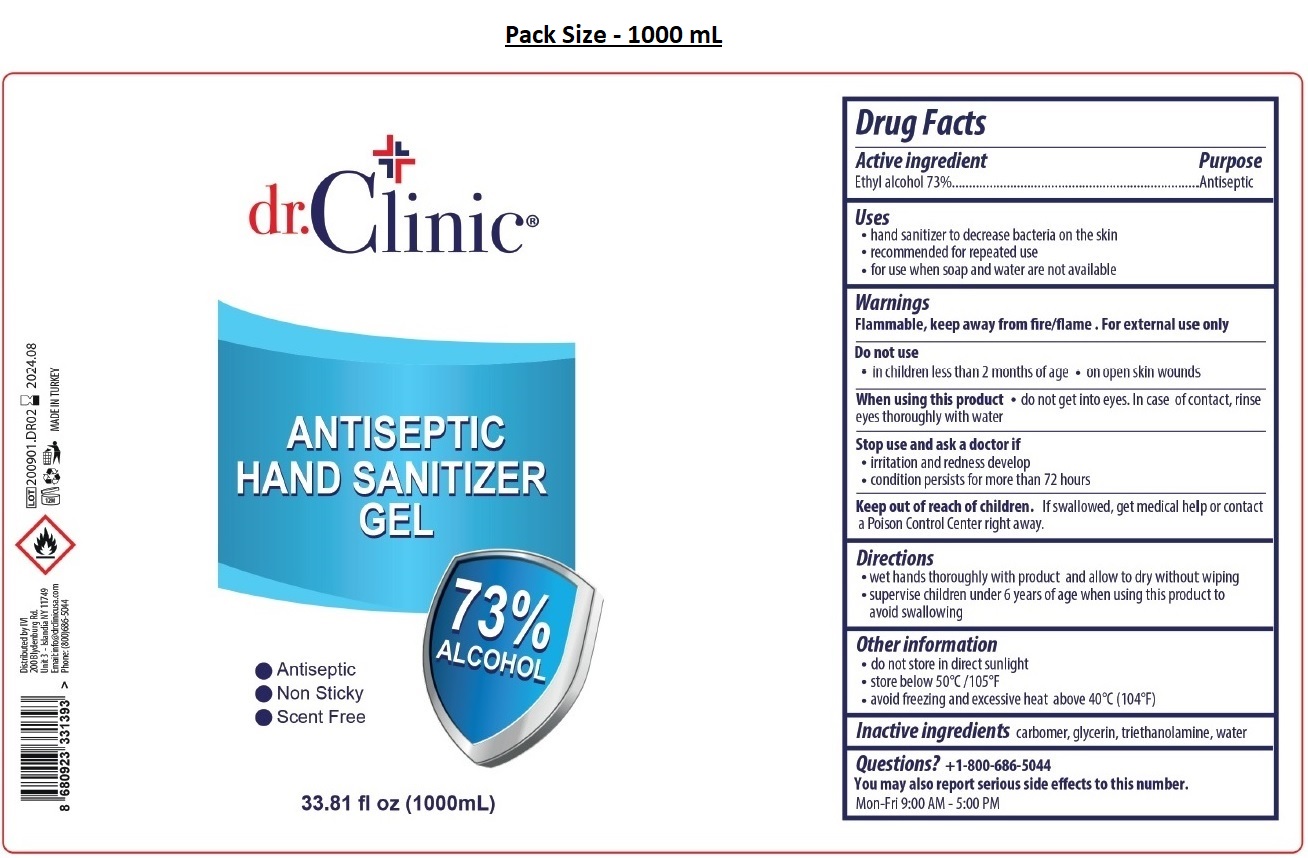 DRUG LABEL: DR CLINIC ANTISEPTIC HAND Gel
NDC: 76725-011 | Form: GEL
Manufacturer: MAKYAJ KOZMETIK INSAAT SANAYI VE TICARET LIMITED SIRKETI
Category: otc | Type: HUMAN OTC DRUG LABEL
Date: 20200910

ACTIVE INGREDIENTS: ALCOHOL 73 mL/100 mL
INACTIVE INGREDIENTS: CARBOMER HOMOPOLYMER, UNSPECIFIED TYPE; GLYCERIN; TROLAMINE; WATER

dr.Clinic® ANTISEPTIC HAND SANITIZER GEL

Active ingredient

Ethyl alcohol 73%

Purpose

Antiseptic

Uses

• hand sanitizer to decrease bacteria on the skin
• recommended for repeated use
• for use when soap and water are not available

Warnings

Flammable, keep away from fire/flame. For external use only
Do not use
• in children less than 2 months of age • on open skin wounds
When using this product • do not get into eyes. In case of contact, rinse eyes thoroughly with water
Stop use and ask a doctor if
• irritation and redness develop
• condition persists for more than 72 hours

Keep out of reach of children. If swallowed, get medical help or contact a Poison Control Center right away.

Directions

• wet hands thoroughly with product and allow to dry without wiping
• supervise children under 6 years of age when using this product to avoid swallowing

Other information

• do not store in direct sunlight
• store below 50°C/105°F
• avoid freezing and excessive heat above 40°C (104°F)

Inactive ingredients carbomer, glycerin, triethanolamine, water

Question? +1-800-686-5044

You may also report serious side effects to this number.
Mon-Fri 9.00 AM - 5.00 PM

73% ALCOHOL

Antiseptic

Non Sticky

Scent Free

Distributed by IVI

200 Blydenburg Rd.

Unit 3 - Islandia NY 11749

Email:info@drclinicusa.com

Phone: (800)686-5044

MADE IN TURKEY